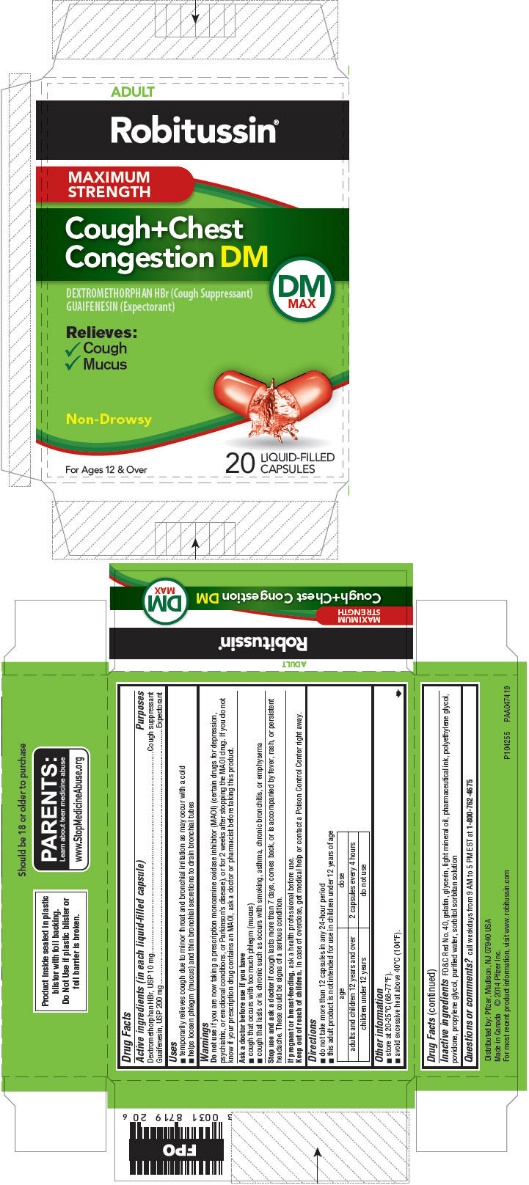 DRUG LABEL: Robitussin Maximum Strength Cough Plus Chest Congestion DM
NDC: 0031-8719 | Form: CAPSULE, LIQUID FILLED
Manufacturer: Haleon US Holdings LLC
Category: otc | Type: HUMAN OTC DRUG LABEL
Date: 20260108

ACTIVE INGREDIENTS: DEXTROMETHORPHAN HYDROBROMIDE 10 mg/1 1; GUAIFENESIN 200 mg/1 1
INACTIVE INGREDIENTS: FD&C RED NO. 40; GELATIN, UNSPECIFIED; GLYCERIN; LIGHT MINERAL OIL; POLYETHYLENE GLYCOL, UNSPECIFIED; POVIDONE, UNSPECIFIED; PROPYLENE GLYCOL; WATER; SORBITOL; SORBITAN

Drug Facts

Active ingredients (in each liquid-filled capsule)

Dextromethorphan HBr, USP 10 mg

Guaifenesin, USP 200 mg

Purposes

Cough suppressant

Expectorant

Uses

- temporarily relieves cough due to minor throat and bronchial irritation as may occur with a cold
- helps loosen phlegm (mucus) and thin bronchial secretions to drain bronchial tubes

Warnings

Do not use if you are now taking a prescription monoamine oxidase inhibitor (MAOI) (certain drugs for depression, psychiatric, or emotional conditions, or Parkinson's disease), or for 2 weeks after stopping the MAOI drug. If you do not know if your prescription drug contains an MAOI, ask a doctor or pharmacist before taking this product.

Ask a doctor before use if you have

- cough that occurs with too much phlegm (mucus)
- cough that lasts or is chronic such as occurs with smoking, asthma, chronic bronchitis, or emphysema

Stop use and ask a doctor if cough lasts more than 7 days, comes back, or is accompanied by fever, rash, or persistent headache. These could be signs of a serious condition.

PREGNANCY OR BREAST FEEDING

If pregnant or breast-feeding, ask a health professional before use.

Keep out of reach of children. In case of overdose, get medical help or contact a Poison Control Center right away.

Directions

- do not take more than 12 capsules in any 24-hour period
- this adult product is not intended for use in children under 12 years of age

age | dose
adults and children 12 years and over | 2 capsules every 4 hours
children under 12 years | do not use

Other information

- store at 20-25°C (68-77°F).
- avoid excessive heat above 40°C (104°F).

Inactive ingredients

FD&C Red No. 40, gelatin, glycerin, light mineral oil, pharmaceutical ink, polyethylene glycol, povidone, propylene glycol, purified water, sorbitol sorbitan solution

Questions or comments?

call weekdays from 9 AM to 5 PM EST at 1-800-762-4675

Made in Canada

For most recent product information, visit www.robitussin.com

Distributed by: Pfizer, Madison, NJ 07940 USA

PRINCIPAL DISPLAY PANEL

ADULT

Robitussin®

MAXIMUM
STRENGTH

Cough+Chest
Congestion DM

DEXTROMETHORPHAN HBr (Cough Suppressant)
GUAIFENESIN (Expectorant)

DM
MAX

Relieves:

- Cough
- Mucus

Non-Drowsy

For Ages 12 & Over

20
LIQUID-FILLED
CAPSULES